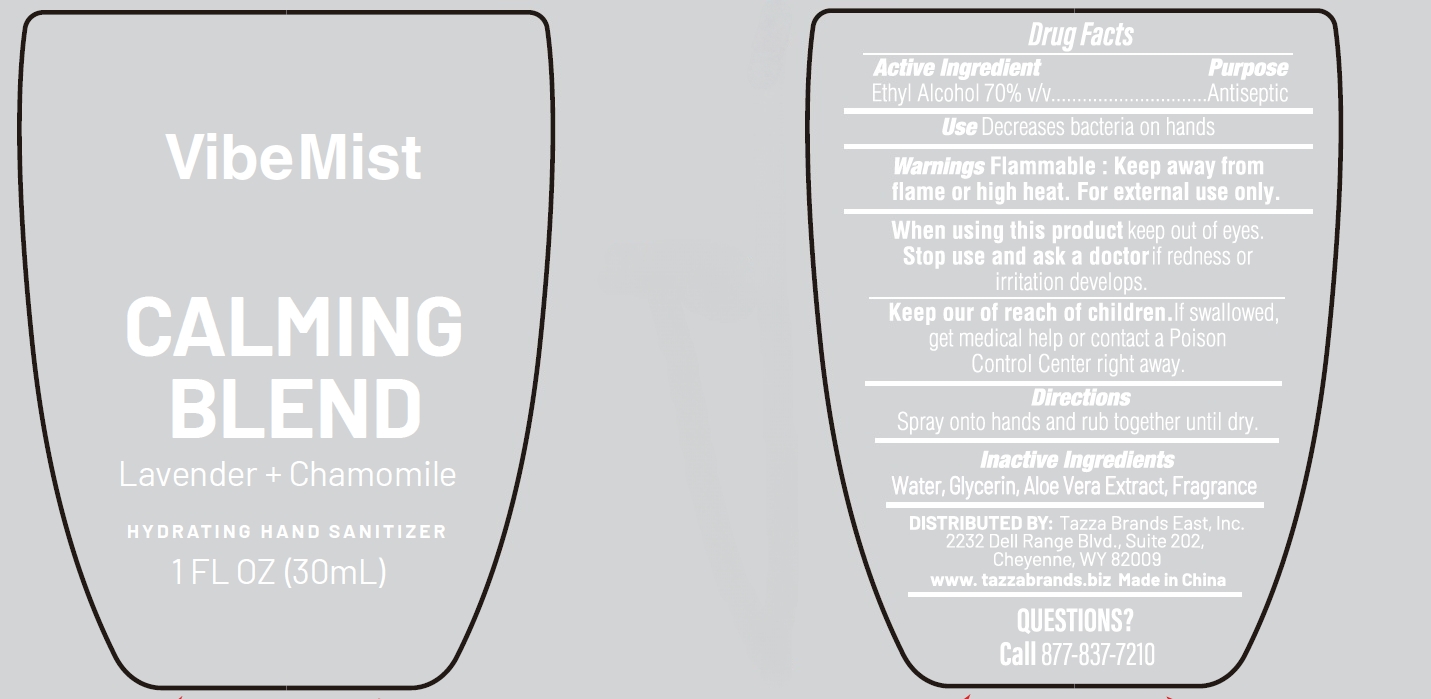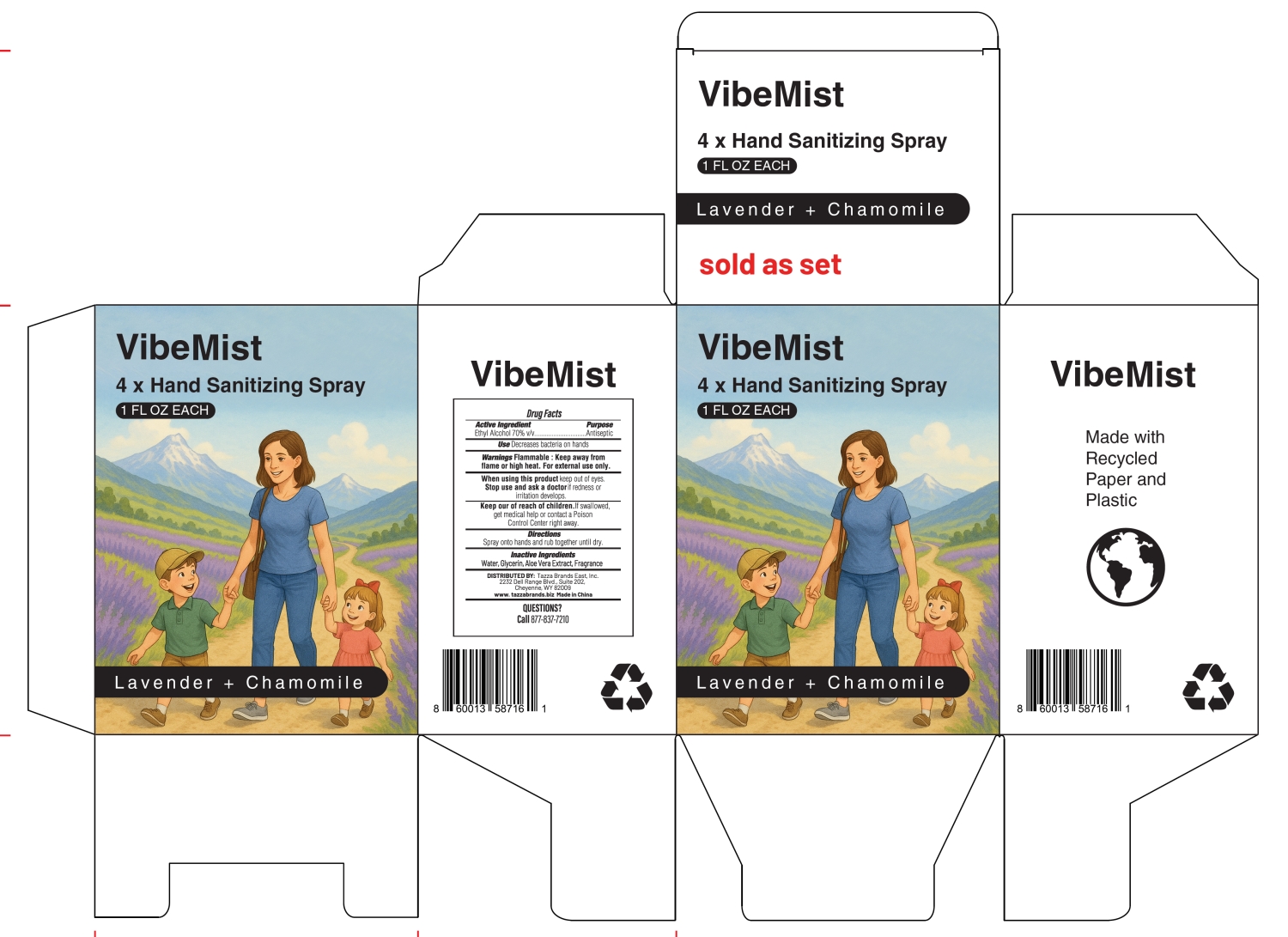 DRUG LABEL: VibeMist HYDRATING HAND SANITIZER Lavender Chamomile
NDC: 76370-0035 | Form: LIQUID
Manufacturer: Tazza Brands East Inc.
Category: otc | Type: HUMAN OTC DRUG LABEL
Date: 20251225

ACTIVE INGREDIENTS: ALCOHOL 70 mL/100 mL
INACTIVE INGREDIENTS: FRAGRANCE LAVENDER ORC1800979; WATER; GLYCERIN; ALOE VERA LEAF

76370-0035 VibeMist HYDRATING HAND SANITIZER Lavender + Chamomile

Active Ingredient

Ethyl Alcohol 70% v/v

Purpose

Antiseptic

INDICATIONS AND USAGE

Uses Decreases bacteria on hands

WARNINGS

Warnings Flammable: Keep away from flame or high heat. For external use only.

When using this product keep out of eyes.

Stop use and ask a doctor if redness or irritation develops.

Keep out of reach of children. If swallowed, get medical help or contact a Poison Control Center right away.

Directions

Spray onto hand and rub together until dry.

Inactive Ingredients

Water, Glycerin, Aloe Vera Extract, Fragrance

PACKAGE LABEL

VibeMist

CALMING

BLEND

Lavender + Chamomile

HYDRATING HAND SANITIZER

1 FL OZ (30mL)

NDC: 76370-0035-0

VibeMist

4 × Hand Sanitizing Spray

1 FL OZ EACH

Lavender + Chamomile

Sold as set

NDC: 76370-0035-1